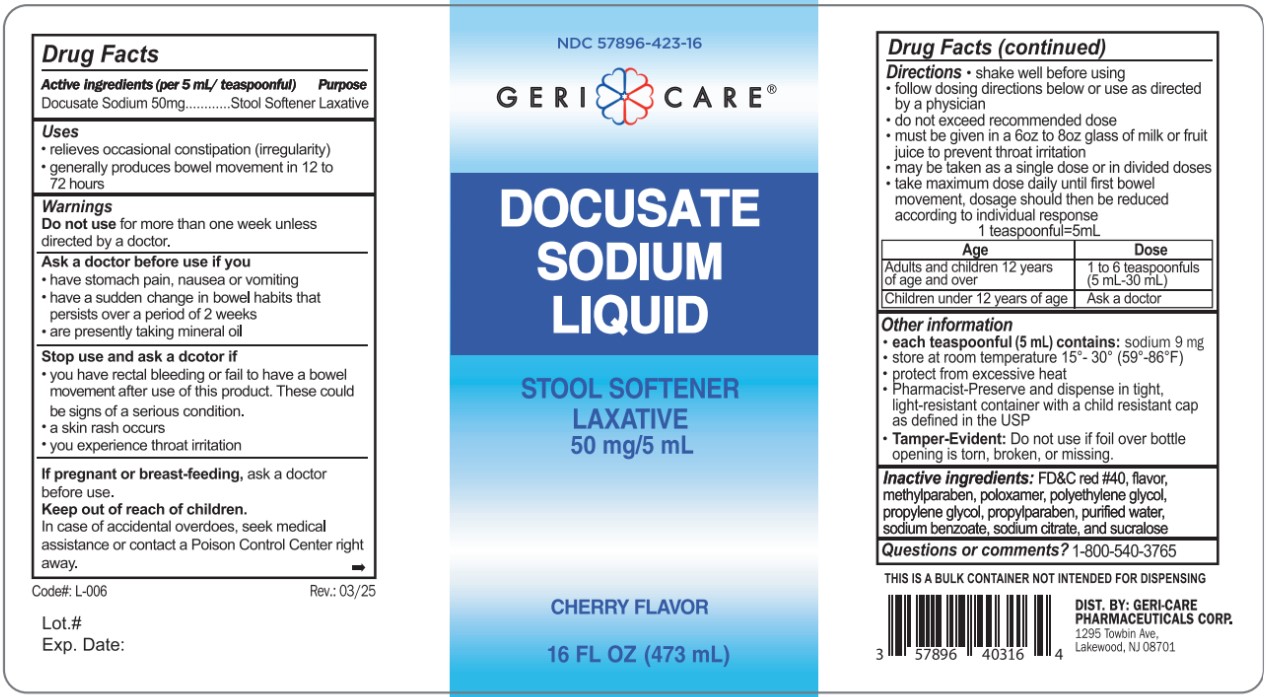 DRUG LABEL: GeriCare Docusate Sodium Liquid
NDC: 57896-423 | Form: LIQUID
Manufacturer: GERI-CARE PHARMACEUTICALS, CORP
Category: otc | Type: HUMAN OTC DRUG LABEL
Date: 20251211

ACTIVE INGREDIENTS: DOCUSATE SODIUM 50 mg/5 mL
INACTIVE INGREDIENTS: FD&C RED NO. 40; METHYLPARABEN; POLOXAMER 124; POLYETHYLENE GLYCOL, UNSPECIFIED; PROPYLENE GLYCOL; PROPYLPARABEN; WATER; SODIUM BENZOATE; SODIUM CITRATE; SUCRALOSE

Geri Care Docusate Sodium Liquid

Active Ingredients (per 5 mL)

Docusate Sodium 50 mg

Purpose

Stool Softener

Uses

- relieves of occasional constipation (irregularity)
- generally produces bowel movement in 12 to 72 hours

Warnings

Do not use for more than one week unless directed by a doctor.

Ask a doctore before use if you

- have stomach pain, nausea or vomiting
- hadve sudden change in bowel habits that persits over a period of 2 weeks
- are taking mineral oil

Stop use and ask doctor if

- you have rectal bleeding or fail to have a bowel movement afrer use of this product. These could be signs of a serious condition.
- a skin rash occurs
- you experience throat irritation

PREGNANCY OR BREAST FEEDING

If pregnant or breast-feeding, ask a doctor before use

Keep out of reach of children. In case of accidental overdose, seek medical assistance or contact a Poison Control Center right away.

Directions

shake well before using

- follow dosing directions below or use as directed by a physician
- do not exceed recommended dose
- must be given in a 6 oz to 8 oz glass of milk or fruit juice to prevent throat irritation
- may be taken as a single daily dose or in dividend dose
- take maximum dose daily until first bowel movement, dosage should then be reduced according to individual response

1 teasponnful = 5 mL

Age | Dose
Adults and children over 12 years of age | 1 to 6 teaspoons (5 mL - 30 mL)
Children under 12 years of age | Ask a doctor

OTHER INFORMATION

- each teaspoonful (5 mL) contains: sodium 9 mg
- store at room temperature 15°- 30° (59°-86°F)
- protect from excessive heat
- Pharmacist-Preserve and dispense in tight, light-resistant container with a child resistant cap as defined in the USP
- Tamper-Evident: Do not use if foil over bottle opening is torn, broken, or missing

INACTIVE INGREDIENT

Inactive ingredients: FD&C red #40, flavor, methylparaben, poloxamer, polyethylene glycol, propylene glycol, propylparaben, sodium benzoate, sodium citrate, sucralose

Questions or comments? 1-800-540-3765

PACKAGE LABEL

NDC

NDC 57896-423-16

Geri Care

Docusate Sodium Liquid

Stool Softener

Laxative

50 mg/5 mL

Cherry Flavor

Code# L-006

Rev.:03/25